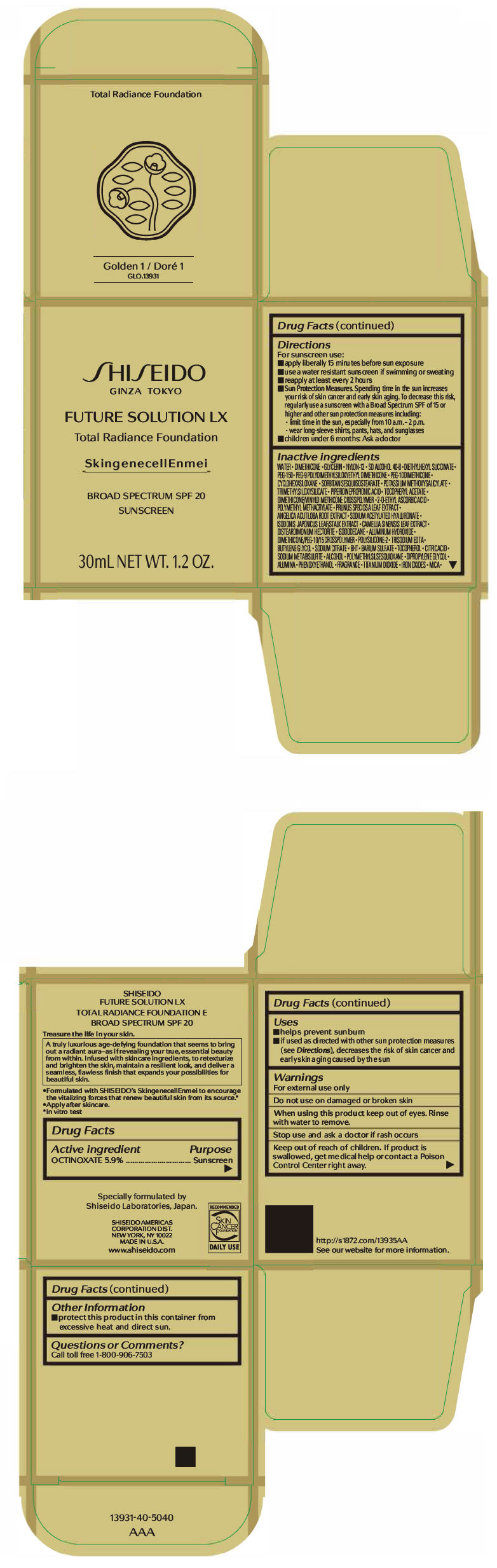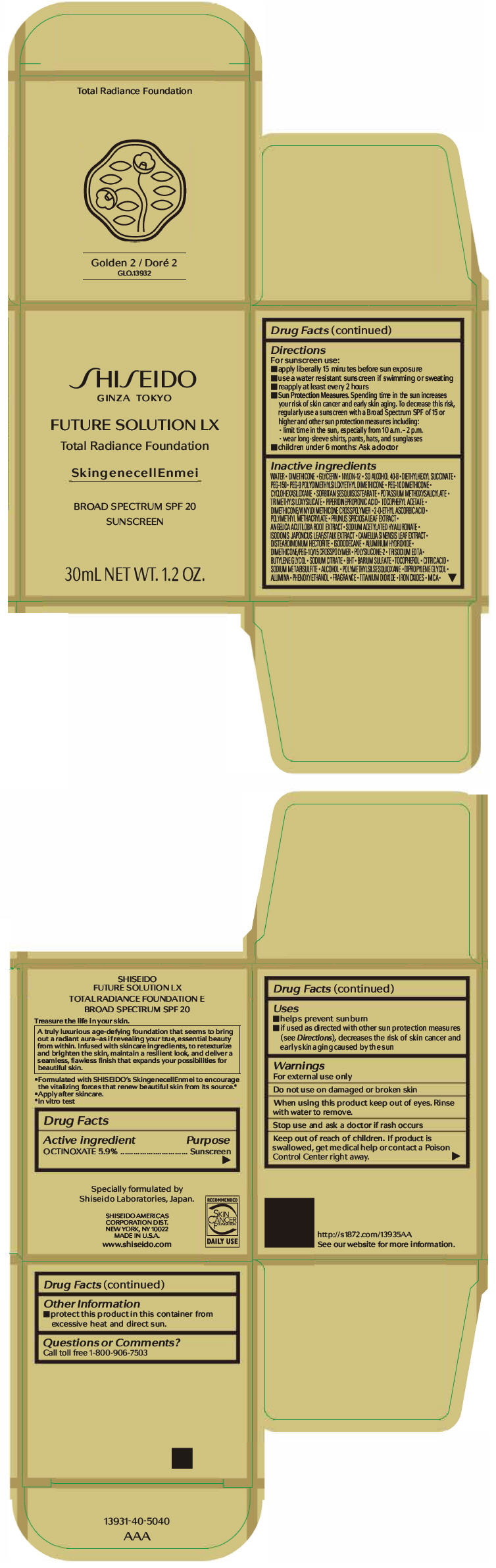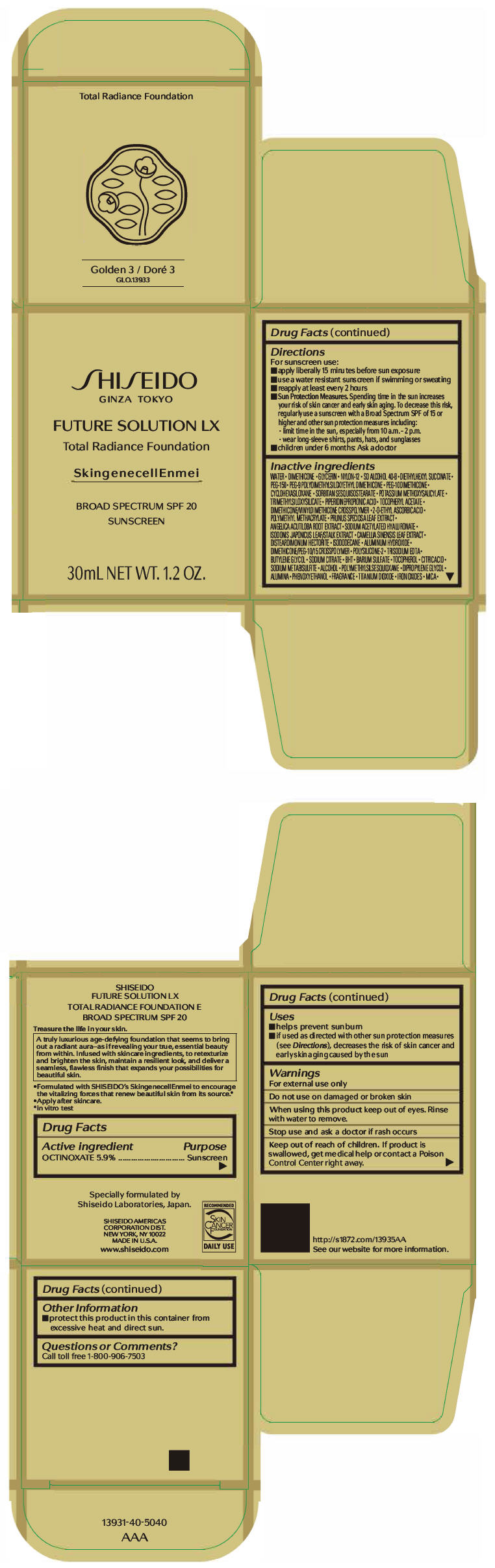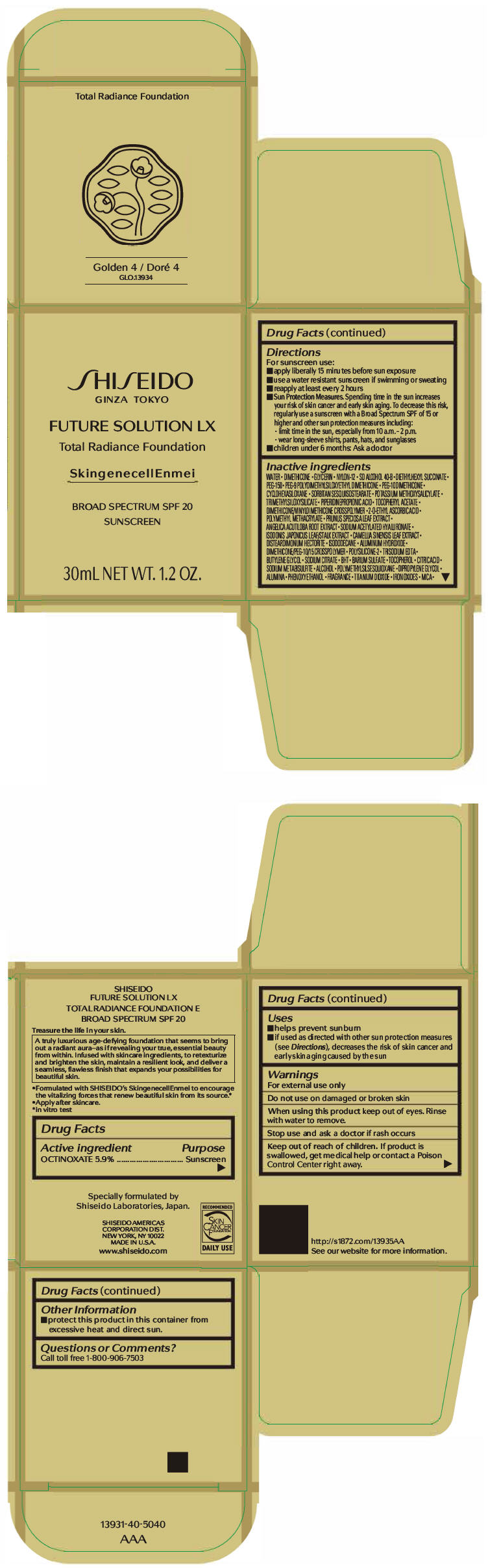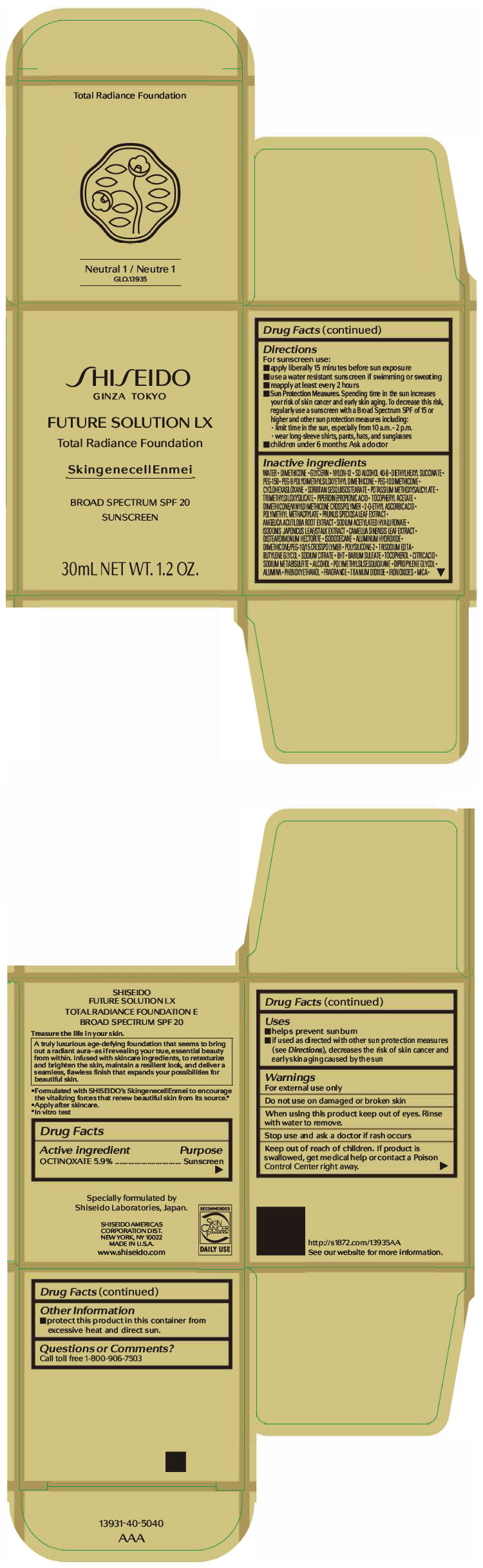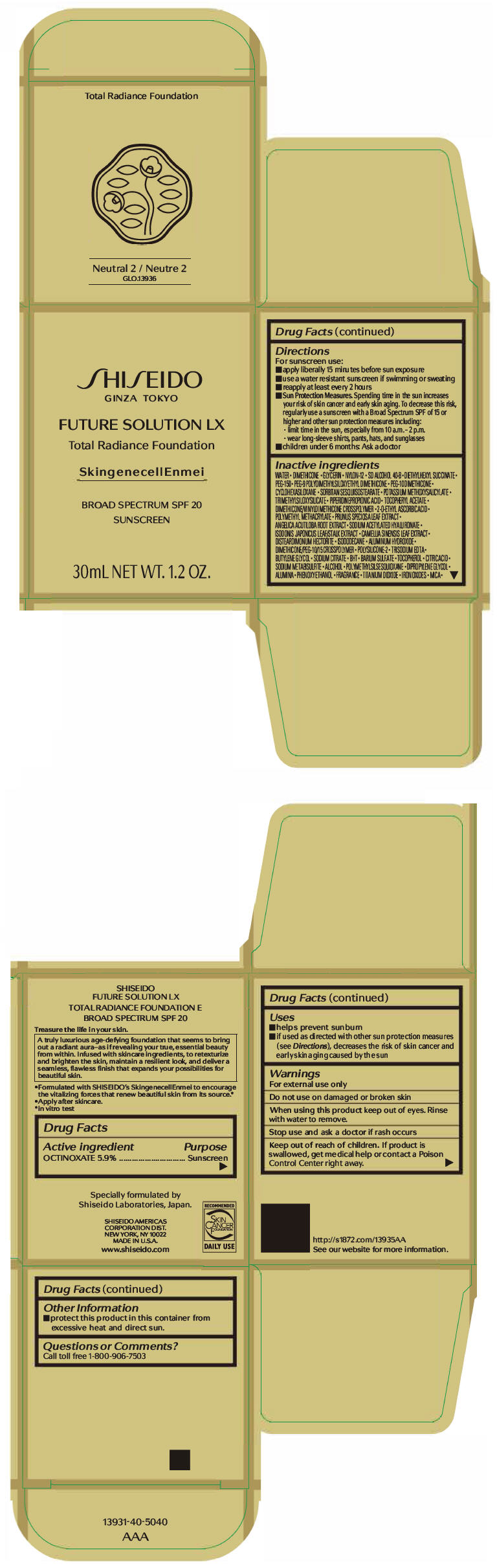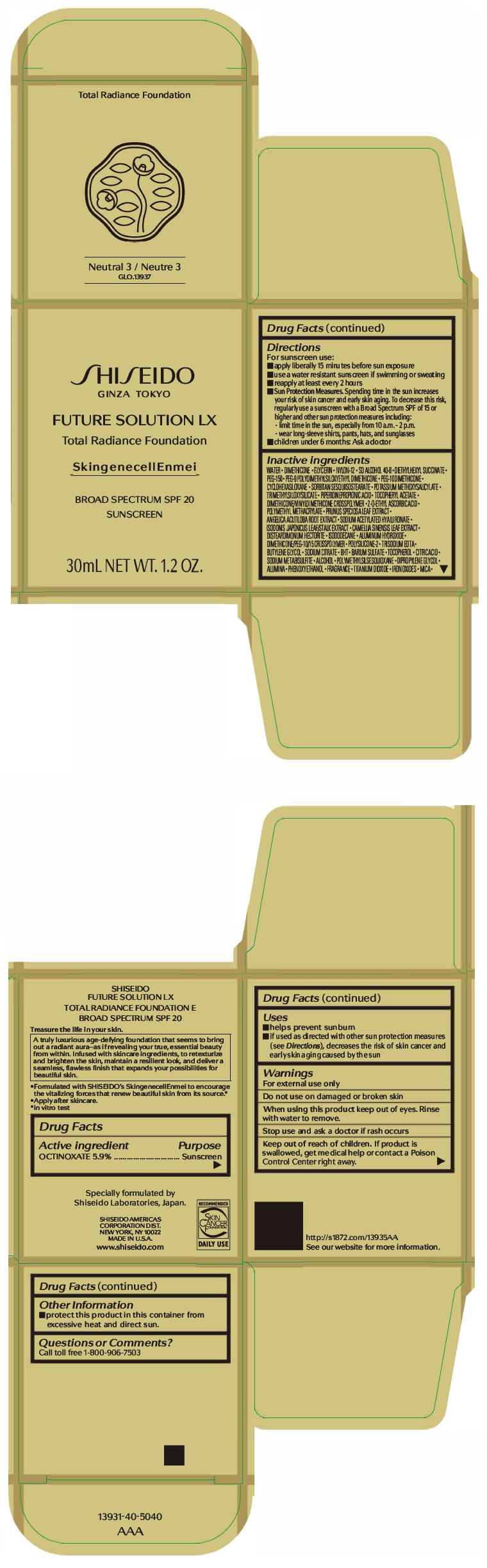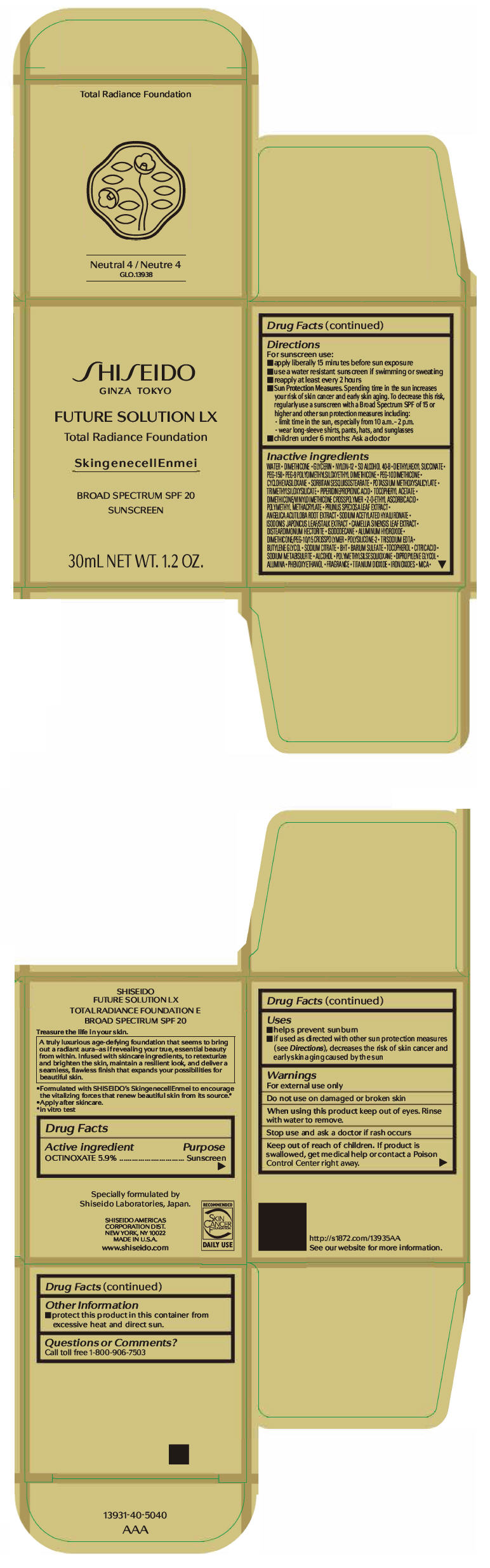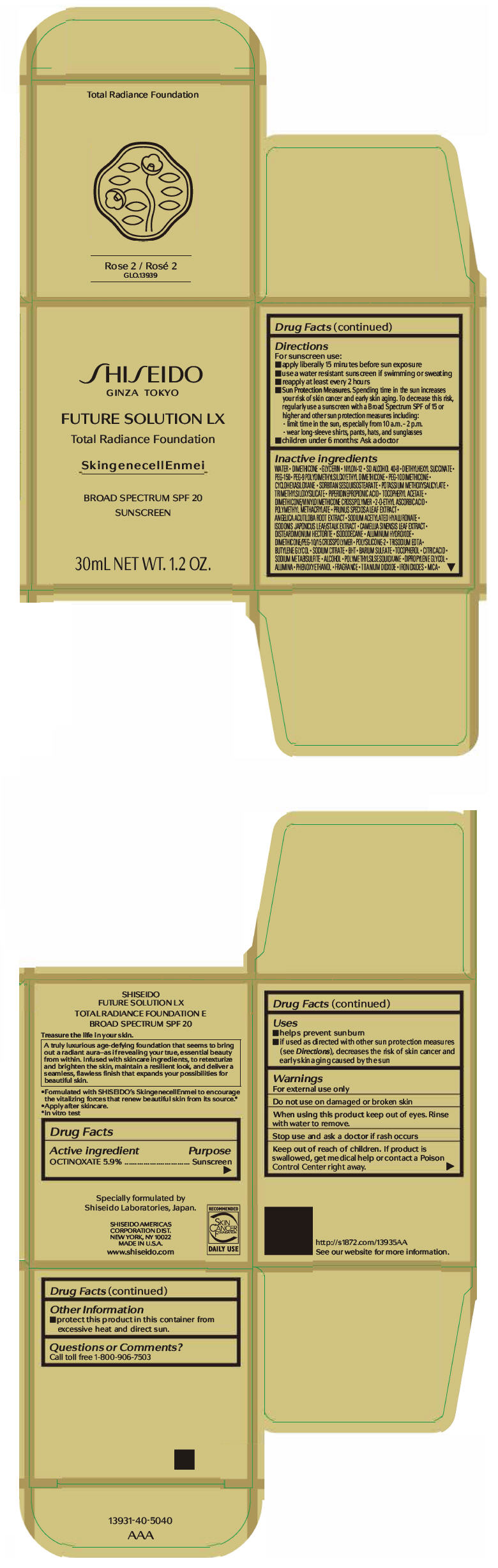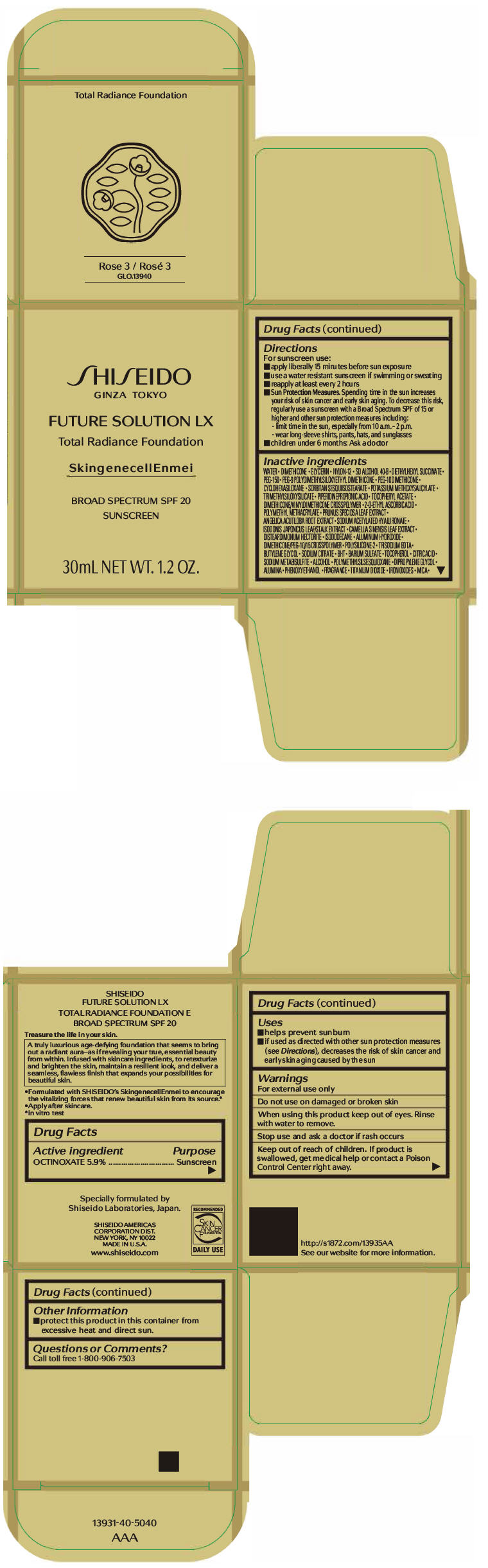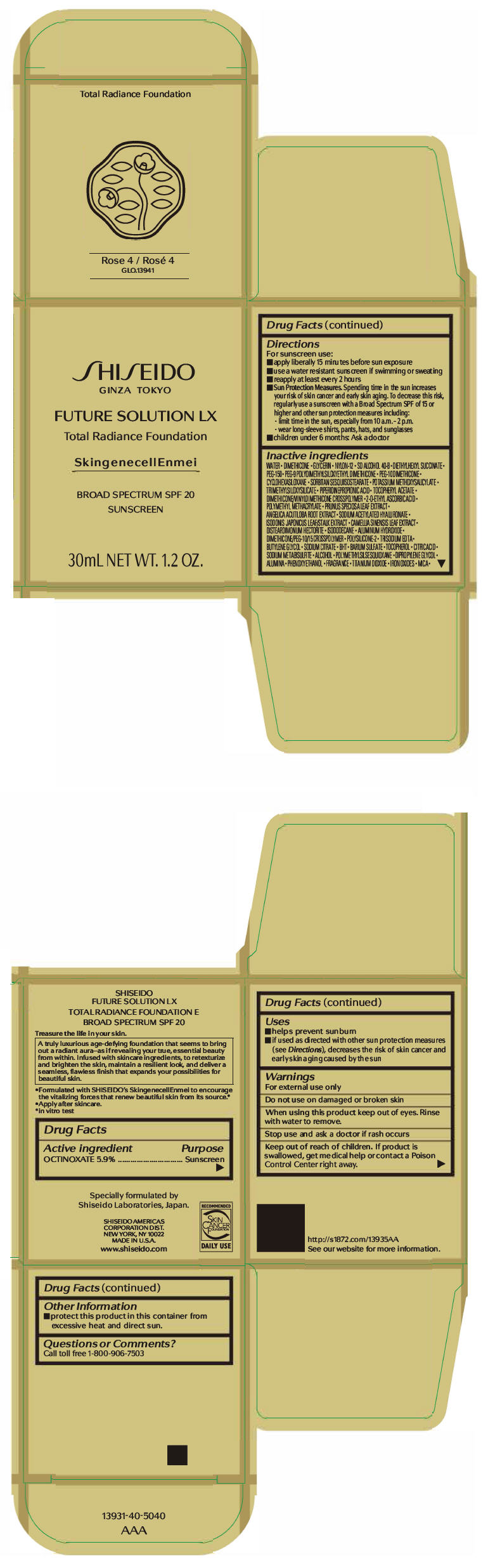 DRUG LABEL: SHISEIDO FUTURE LX TOTAL RADIANCE FOUNDATION E

NDC: 58411-329 | Form: CREAM
Manufacturer: SHISEIDO AMERICAS CORPORATION
Category: otc | Type: HUMAN OTC DRUG LABEL
Date: 20260105

ACTIVE INGREDIENTS: OCTINOXATE 2036 mg/30 mL
INACTIVE INGREDIENTS: WATER; DIMETHICONE; GLYCERIN; NYLON-12; DIETHYLHEXYL SUCCINATE; POLYETHYLENE GLYCOL 7000; PEG-9 POLYDIMETHYLSILOXYETHYL DIMETHICONE; PEG-10 DIMETHICONE (600 CST); CYCLOMETHICONE 6; POTASSIUM METHOXYSALICYLATE; TRIMETHYLSILOXYSILICATE (M/Q 0.6-0.8); PIPERIDINEPROPIONIC ACID; .ALPHA.-TOCOPHEROL ACETATE, DL-; DIMETHICONE/VINYL DIMETHICONE CROSSPOLYMER (SOFT PARTICLE); 2-O-ETHYL ASCORBIC ACID; POLY(METHYL METHACRYLATE; 450000 MW); PRUNUS SPECIOSA LEAF; ANGELICA ACUTILOBA ROOT; SODIUM ACETYLATED HYALURONATE; GREEN TEA LEAF; DISTEARDIMONIUM HECTORITE; ISODODECANE; ALUMINUM HYDROXIDE; EDETATE TRISODIUM; BUTYLENE GLYCOL; SODIUM CITRATE, UNSPECIFIED FORM; BUTYLATED HYDROXYTOLUENE; BARIUM SULFATE; .ALPHA.-TOCOPHEROL; CITRIC ACID MONOHYDRATE; SODIUM METABISULFITE; ALCOHOL; POLYMETHYLSILSESQUIOXANE (4.5 MICRONS); DIPROPYLENE GLYCOL; ALUMINUM OXIDE; PHENOXYETHANOL; TITANIUM DIOXIDE; FERRIC OXIDE RED; FERRIC OXIDE YELLOW; FERROSOFERRIC OXIDE; MICA

SHISEIDO FUTURE SOLUTION LX TOTAL RADIANCE FOUNDATION E

Drug Facts

Active ingredients

OCTINOXATE 5.9%

Purpose

Sunscreen

Uses

- helps prevent sunburn
- if used as directed with other sun protection measures (see Directions), decreases the risk of skin cancer and early skin aging caused by the sun

Warnings

For external use only

Do not useon damaged or broken skin

WHEN USING

When using this productkeep out of eyes. Rinse with water to remove.

Stop use and ask a doctorif rash occurs

Keep out of reach of children.If product is swallowed, get medical help or contact a Poison Control Center right away.

Directions

For sunscreen use:

- apply liberally 15 minutes before sun exposure
- use a water resistant sunscreen if swimming or sweating
- reapply at least every 2 hours
- Sun Protection Measures. Spending time in the sun increases your risk of skin cancer and early skin aging. To decrease this risk, regularly use a sunscreen with a broad spectrum SPF of 15 or higher and other sun protection measures including:
  - limit time in the sun, especially from 10 a.m. – 2 p.m.
  - wear long-sleeve shirts, pants, hats, and sunglasses
- children under 6 months: Ask a doctor

Inactive Ingredients

WATER∙DIMETHICONE∙GLYCERIN∙NYLON-12∙SD ALCOHOL 40-B∙DIETHYLHEXYL SUCCINATE∙PEG-150∙PEG-9 POLYDIMETHYLSILOXYETHYL DIMETHICONE∙PEG-10 DIMETHICONE∙CYCLOHEXASILOXANE∙SORBITAN SESQUIISOSTEARATE∙POTASSIUM METHOXYSALICYLATE∙TRIMETHYLSILOXYSILICATE∙PIPERIDINEPROPIONIC ACID∙TOCOPHERYL ACETATE∙DIMETHICONE/VINYL DIMETHICONE CROSSPOLYMER∙2-O-ETHYL ASCORBIC ACID∙POLYMETHYL METHACRYLATE∙PRUNUS SPECIOSA LEAF EXTRACT∙ANGELICA ACUTILOBA ROOT EXTRACT∙SODIUM ACETYLATED HYALURONATE∙ISODONIS JAPONICUS LEAF/STALK EXTRACT∙CAMELLIA SINENSIS LEAF EXTRACT∙DISTEARDIMONIUM HECTORITE∙ISODODECANE∙ALUMINUM HYDROXIDE∙DIMETHICONE/PEG-10/15 CROSSPOLYMER∙POLYSILICONE-2∙TRISODIUM EDTA∙BUTYLENE GLYCOL∙SODIUM CITRATE∙BHT∙BARIUM SULFATE∙TOCOPHEROL∙CITRIC ACID∙SODIUM METABISULFITE∙ALCOHOL∙POLYMETHYLSILSESQUIOXANE∙DIPROPYLENE GLYCOL∙ALUMINA∙PHENOXYETHANOL∙FRAGRANCE∙TITANIUM DIOXIDE∙IRON OXIDES∙MICA∙

Other information

- protect this product in this container from excessive heat and direct sun.

Questions or comments?

Call toll free 1-800-906-7503

PRINCIPAL DISPLAY PANEL - 30 mL Jar Carton - Golden 1

SHI SEIDO
GINZA TOKYO

FUTURE SOLUTION LX
Total Radiance Foundation

SkingenecellEnmei

BROAD SPECTRUM SPF 20
SUNSCREEN

30mL NET WT. 1.2 OZ.

PRINCIPAL DISPLAY PANEL - 30 mL Jar Carton - Golden 2

SHI SEIDO
GINZA TOKYO

FUTURE SOLUTION LX
Total Radiance Foundation

SkingenecellEnmei

BROAD SPECTRUM SPF 20
SUNSCREEN

30mL NET WT. 1.2 OZ.

PRINCIPAL DISPLAY PANEL - 30 mL Jar Carton - Golden 3

SHI SEIDO
GINZA TOKYO

FUTURE SOLUTION LX
Total Radiance Foundation

SkingenecellEnmei

BROAD SPECTRUM SPF 20
SUNSCREEN

30mL NET WT. 1.2 OZ.

PRINCIPAL DISPLAY PANEL - 30 mL Jar Carton - Golden 4

SHI SEIDO
GINZA TOKYO

FUTURE SOLUTION LX
Total Radiance Foundation

SkingenecellEnmei

BROAD SPECTRUM SPF 20
SUNSCREEN

30mL NET WT. 1.2 OZ.

PRINCIPAL DISPLAY PANEL - 30 mL Jar Carton - Neutral 1

SHI SEIDO
GINZA TOKYO

FUTURE SOLUTION LX
Total Radiance Foundation

SkingenecellEnmei

BROAD SPECTRUM SPF 20
SUNSCREEN

30mL NET WT. 1.2 OZ.

PRINCIPAL DISPLAY PANEL - 30 mL Jar Carton - Neutral 2

SHI SEIDO
GINZA TOKYO

FUTURE SOLUTION LX
Total Radiance Foundation

SkingenecellEnmei

BROAD SPECTRUM SPF 20
SUNSCREEN

30mL NET WT. 1.2 OZ.

PRINCIPAL DISPLAY PANEL - 30 mL Jar Carton - Neutral 3

SHI SEIDO
GINZA TOKYO

FUTURE SOLUTION LX
Total Radiance Foundation

SkingenecellEnmei

BROAD SPECTRUM SPF 20
SUNSCREEN

30mL NET WT. 1.2 OZ.

PRINCIPAL DISPLAY PANEL - 30 mL Jar Carton - Neutral 4

SHI SEIDO
GINZA TOKYO

FUTURE SOLUTION LX
Total Radiance Foundation

SkingenecellEnmei

BROAD SPECTRUM SPF 20
SUNSCREEN

30mL NET WT. 1.2 OZ.

PRINCIPAL DISPLAY PANEL - 30 mL Jar Carton - Rose 2

SHI SEIDO
GINZA TOKYO

FUTURE SOLUTION LX
Total Radiance Foundation

SkingenecellEnmei

BROAD SPECTRUM SPF 20
SUNSCREEN

30mL NET WT. 1.2 OZ.

PRINCIPAL DISPLAY PANEL - 30 mL Jar Carton - Rose 3

SHI SEIDO
GINZA TOKYO

FUTURE SOLUTION LX
Total Radiance Foundation

SkingenecellEnmei

BROAD SPECTRUM SPF 20
SUNSCREEN

30mL NET WT. 1.2 OZ.

PRINCIPAL DISPLAY PANEL - 30 mL Jar Carton - Rose 4

SHI SEIDO
GINZA TOKYO

FUTURE SOLUTION LX
Total Radiance Foundation

SkingenecellEnmei

BROAD SPECTRUM SPF 20
SUNSCREEN

30mL NET WT. 1.2 OZ.